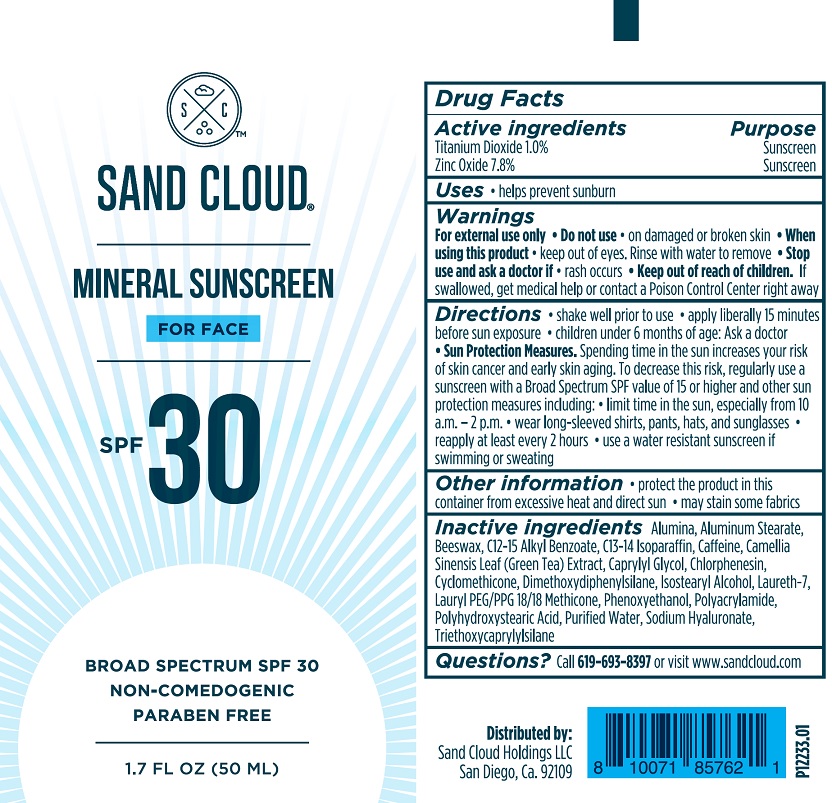 DRUG LABEL: Sand Cloud Mineral Sunscreen For Face
NDC: 83081-2056 | Form: LOTION
Manufacturer: Sand Cloud Holdings, LLC
Category: otc | Type: HUMAN OTC DRUG LABEL
Date: 20251219

ACTIVE INGREDIENTS: ZINC OXIDE 83.4 mg/1 g; TITANIUM DIOXIDE 10 mg/1 g
INACTIVE INGREDIENTS: GREEN TEA LEAF; YELLOW WAX; CAFFEINE; PHENOXYETHANOL; CAPRYLYL GLYCOL; CHLORPHENESIN; LAURYL PEG/PPG-18/18 METHICONE; ALUMINUM OXIDE; HYALURONATE SODIUM; TRIETHOXYCAPRYLYLSILANE; ISOSTEARYL ALCOHOL; ALUMINUM STEARATE; POLYACRYLAMIDE (1500 MW); DIMETHOXYDIPHENYLSILANE; POLYHYDROXYSTEARIC ACID (2300 MW); ALKYL (C12-15) BENZOATE; WATER; CYCLOMETHICONE; C13-14 ISOPARAFFIN; LAURETH-7

Sand Cloud Mineral Sunscreen For Face

Active ingredients

Titanium Dioxide 1.0%

Zinc Oxide 7.8%

Purpose

Sunscreen

Uses

- helps prevent sunburn

Warnings

For external use only

Do not use

- on damaged or broke skin

When using this product

- keep out of eyes. Rinse with water to remove

Stop use and ask a doctor if

- rash occurs

Keep out of reach of children.

If swallowed, get medical help or contact a Poison Control Center right away.

Directions

- shake well prior to use
- apply liberally 15 minutes before sun exposure
- children under 6 months of age: Ask a doctor
- Sun Protection Measures. Spending time in the sun increases your risk of skin cancer and early skin aging. To decrease this risk, regularly use a sunscreen with a Broad Spectrum SPF value of 15 or higher and other sun protection measures including:
- limit time in the sun, especially from 10 a.m. - 2 p.m.
- wear long-sleeved shirts, pants, hats, and sunglasses
- reapply at least every 2 hours
- use a water resistant sunscreen if swimming or sweating

Other information

- protect the product in this container from excessive heat and direct sun
- may stain some fabrics

Inactive ingredients

Alumina, Aluminum Stearate, Beeswax, C12-15 Alkyl Benzoate, C13-14 Isoparaffin, Caffeine, Camellia Sinensis Leaf (Green Tea) Extract, Caprylyl Glycol, Chlorphenesin, Cyclomethicone, Dimethoxydiphenylsilane, Isostearyl Alcohol, Laureth-7, Lauryl PEG/PPG 18/18 Methicone, Phenoxyethanol, Polyacrylamide, Polyhydroxystearic Acid, Purified Water, Sodium Hyaluronate, Triethoxycaprylylsilane

Questions?

Call 619-693-8397 or visit www.sandcloud.com

Sand Cloud Mineral Sunscreen For Face Tube

SAND CLOUD

MINERAL SUNSCREEN

FOR FACE

SPF 30

BROAD SPECTRUM SPF 30

NON-COMEDOGENIC

PARABEN FREE

1.7 FL OZ (50 ML)

P12233.01